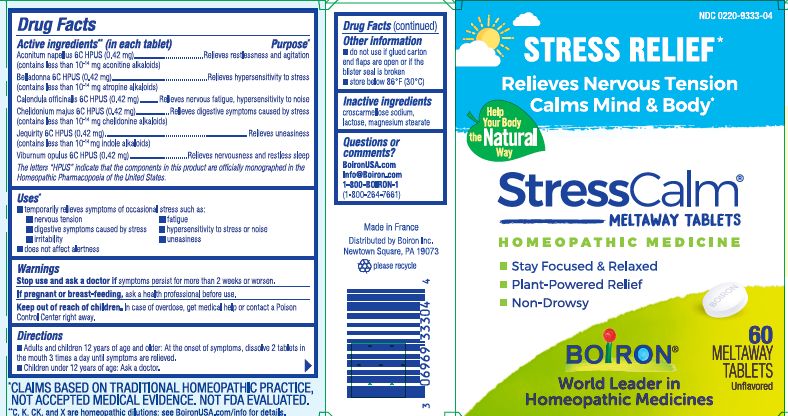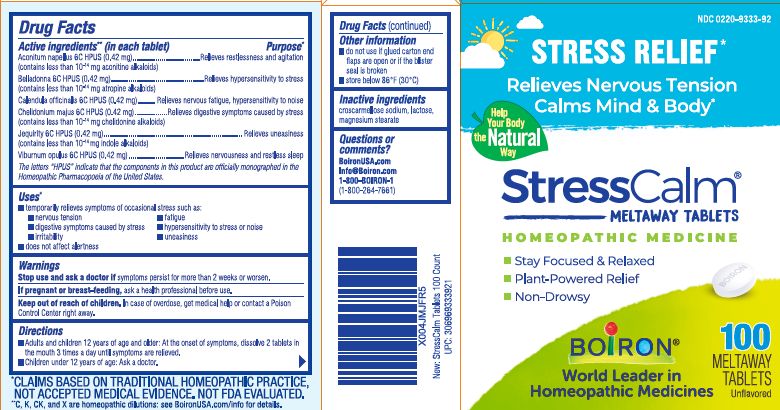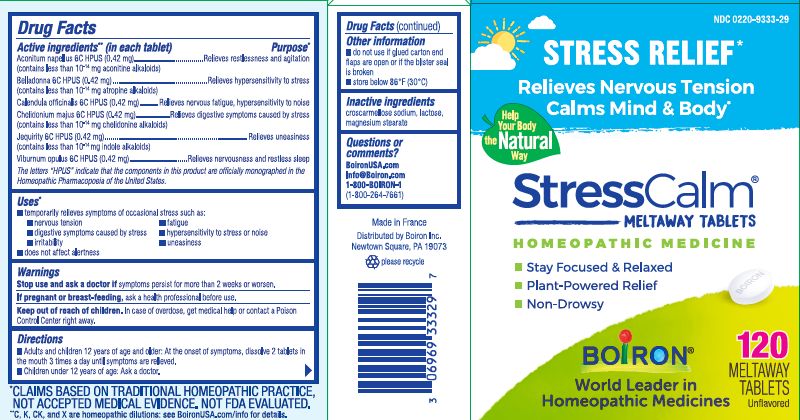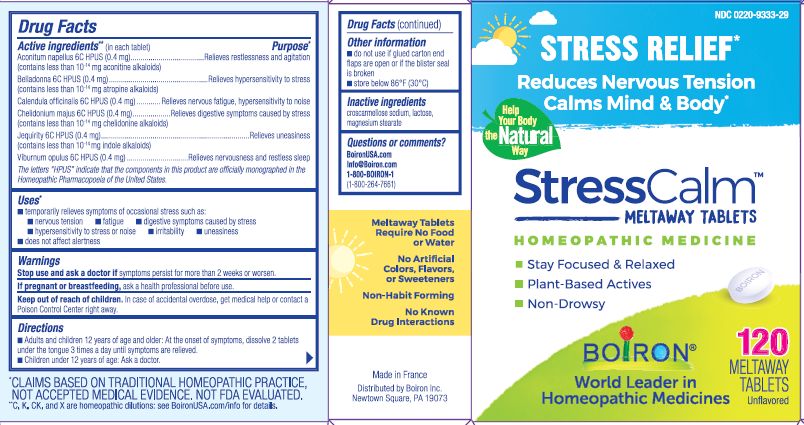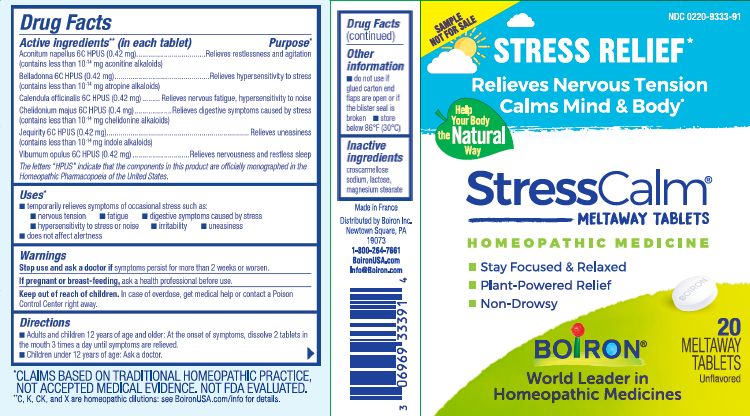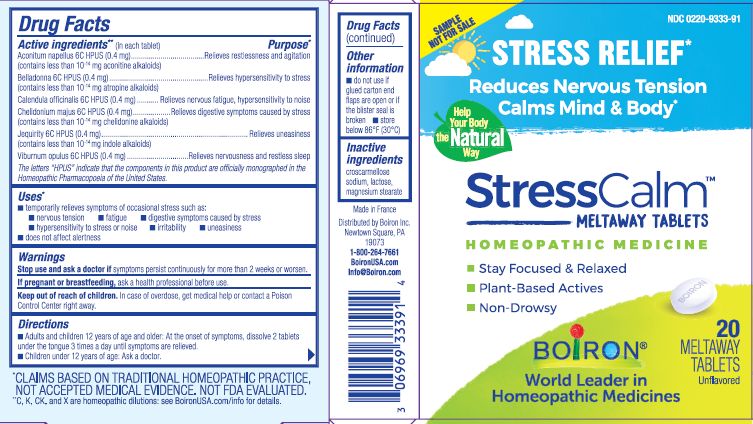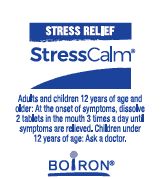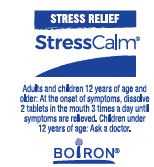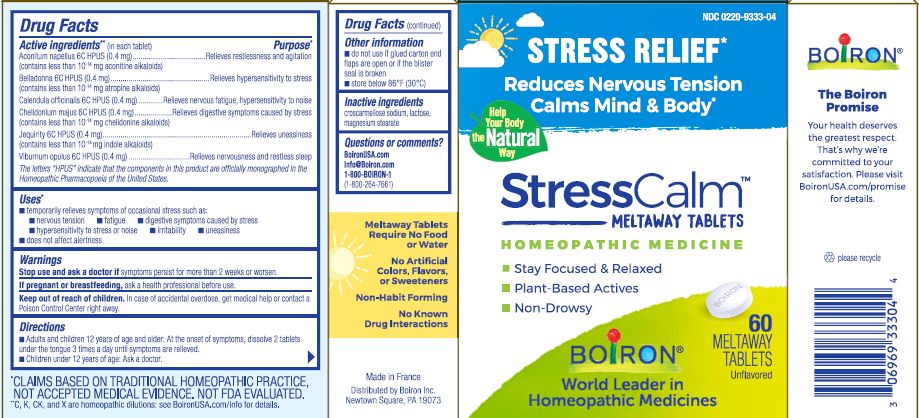 DRUG LABEL: StressCalm
NDC: 0220-9333 | Form: TABLET
Manufacturer: Boiron
Category: homeopathic | Type: HUMAN OTC DRUG LABEL
Date: 20250321

ACTIVE INGREDIENTS: VIBURNUM OPULUS BARK 6 [hp_C]/1 1; ACONITUM NAPELLUS WHOLE 6 [hp_C]/1 1; ATROPA BELLADONNA 6 [hp_C]/1 1; ABRUS PRECATORIUS SEED 6 [hp_C]/1 1; CALENDULA OFFICINALIS FLOWERING TOP 6 [hp_C]/1 1; CHELIDONIUM MAJUS WHOLE 6 [hp_C]/1 1
INACTIVE INGREDIENTS: MAGNESIUM STEARATE; LACTOSE, UNSPECIFIED FORM; CROSCARMELLOSE SODIUM

StressCalm

Active ingredients** (in each tablet)

Aconitum napellus 6C HPUS (0.42 mg) (contains less than 10^-14 mg aconitine alkaloids)

Belladonna 6C HPUS (0.42 mg) (contains less than 10^-14 mg atropine alkaloids)

Calendula officinalis 6C HPUS (0.42 mg)

Chelidonium majus 6C HPUS (0.43 mg) (contains less than 10-^14 mg chelidonine alkaloids)

Jequirity 6C HPUS (0.4 mg) (contains less 10^-14 mg indole alkaloids)

Viburnum opulus 6C HPUS (0.4mg)

The letters "HPUS" indicate that the components in this product are officially monographed in the Homeopathic Pharmacopoeia of the United States.

Purpose*

Aconitum napellus 6C HPUS Relieves restlessness and agitation

Belladonna 6C HPUS Relieves hypersensitivity to stress

Calendula officinalis 6C HPUS Relieves nervous fatigue, hypersensitivity to noise

Chelidonium majus 6C HPUS Relieves digestive symptoms caused by stress

Jequirity 6C HPUS Relieves uneasiness

Viburnum opulus 6C HPUS Relieves nervousness and restless sleep

Uses*

temporarily relieves symptoms of occasional stress such as:

- nervous tension
- fatigue
- digestive symptoms caused by stress
- hypersensitivity to stress or noise
- irritability, uneasiness

does not affect alertness

Stop use and ask a doctor if symptoms persist for more than 2 weeks or worsen.

PREGNANCY OR BREAST FEEDING

If pregnant or breast-feeding, ask a health professional before use.

Keep out of reach of children. In case of accidental overdose, get medical help or contact a Poison Control Center right away.

Directions

Adults and children 12 years of age and older: At the onset of symptoms, dissolve 2 tablets under the tongue 3 times a day until symptoms are relieved.

Children under 12 years of age: Ask a doctor.

Do not use if glued carton end flaps are open or if the blister seal is broken.

store below 86°F (30°C)

contains 20 meltaway tablets unflavored

contains 60 meltaway tablets unflavored

contains 100 meltaway tablets unflavored

contains 120 meltaway tablets unflavored

Stress Relief*

Relieves Nervous Tension Calms Mind & Body*

Non-Drowsy

No known drug interactions

*CLAIMS BASED ON TRADITIONAL HOMEOPATHIC PRACTICE, NOT ACCEPTED MEDICAL EVIDENCE. NOT FDA EVALUATED.
*C,K,CK, and X are homeopathic dilutions: see BoironUSA.com/info for details.

INACTIVE INGREDIENT

croscarmellose sodium, lactose, magnesium stearate

Questions or comments?

1-800-BOIRON-1 (1-800-264-7661),
BoironUSA.com Info@boiron.com
Distributed by Boiron, Inc. Newtown Square, PA 19073